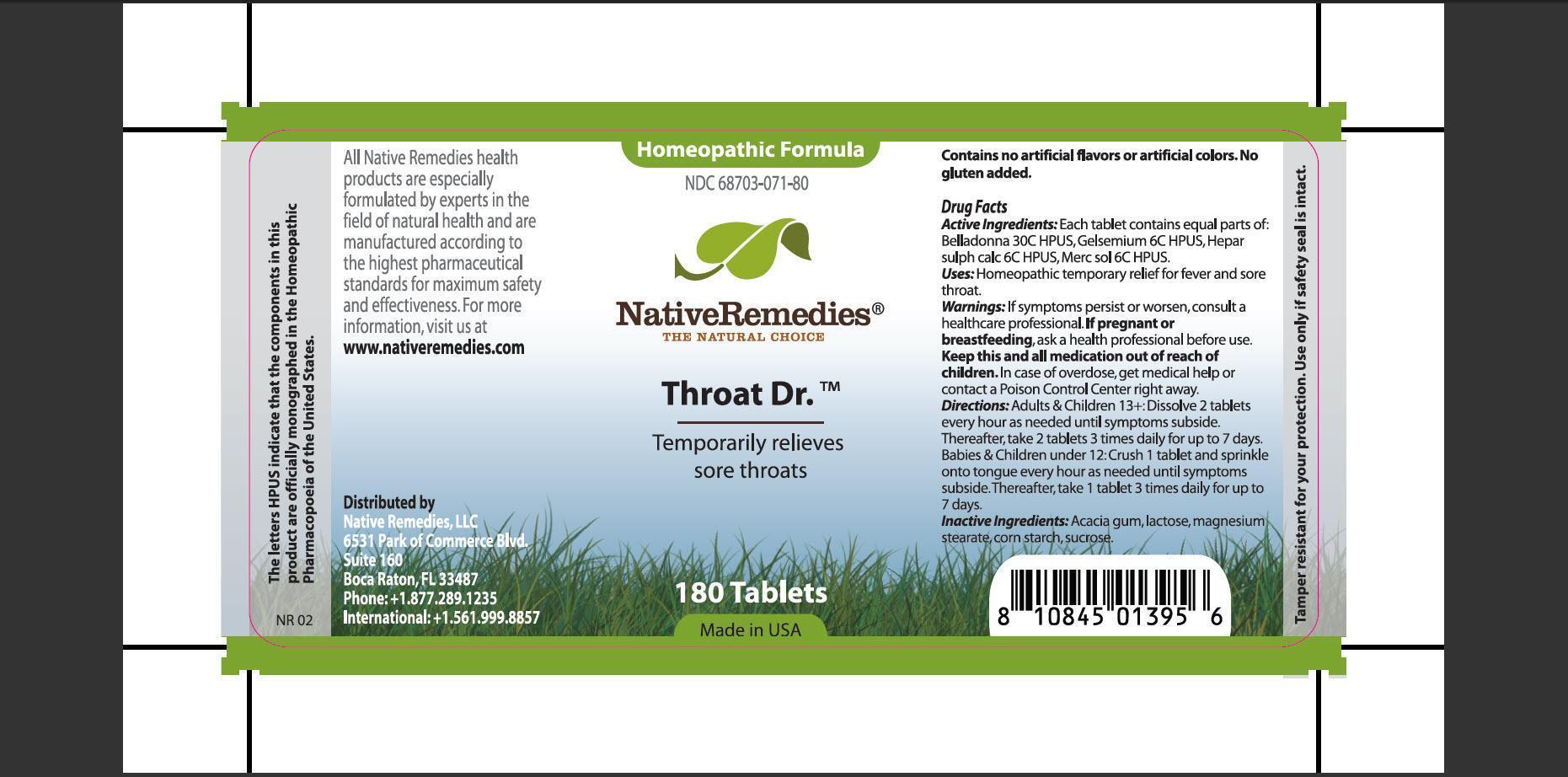 DRUG LABEL: Throar Dr.
NDC: 68703-071 | Form: TABLET
Manufacturer: Native Remedies, LLC
Category: homeopathic | Type: HUMAN OTC DRUG LABEL
Date: 20130124

ACTIVE INGREDIENTS: ATROPA BELLADONNA 30 [hp_C]/1 1; GELSEMIUM SEMPERVIRENS ROOT 6 [hp_C]/1 1; CALCIUM SULFIDE 6 [hp_C]/1 1; MERCURIUS SOLUBILIS 6 [hp_C]/1 1
INACTIVE INGREDIENTS: ACACIA; LACTOSE; MAGNESIUM STEARATE; STARCH, CORN; SUCROSE

Throat Dr.

PURPOSE

Temporarily relieves sore throats

ACTIVE INGREDIENT

Active Ingredients: Each tablet contains equal parts of: Belladonna 30C HPUS, Gelsemium 6C HPUS, Hepar sulph calc 6C HPUS, Merc sol 6C HPUS

INDICATIONS AND USAGE

Uses: Homeopathic temporary relief for fever and sore throat

WARNINGS

Warning: If symptoms persist or worsen, consult a healthcare professional.

PREGNANCY OR BREAST FEEDING

If pregnant or breastfeeding, ask a health professional before use

KEEP OUT OF REACH OF CHILDREN

Keep this and all medication out of reach of children

OVERDOSAGE

In case of overdose, get medical help or contact a Poison Control Center right away.

DOSAGE AND ADMINISTRATION

Directions: Adults and Children 13+: Dissolve 2 tablets every hour as needed until symptoms subside. Thereafter, take 2 tablets 3 times daily for up to 7 days. Babies and Children under 12: Crush 1 tablet and sprinkle onto tongue every hour as needed until symptoms subside. Thereafter, take 1 tablet 3 times daily for up to 7 days.

INACTIVE INGREDIENT

Inactive Ingredients: Acacia gum, lactose, magnesium stearate, corn starch, sucrose

PATIENT COUNSELING INFORMATION

The letters HPUS indicate that the components in this product are officially monographed in the Homeopathic Pharmacopoeia of the United States.

All Native Remedies health products are especially formulated by experts in the field of natural health and are manufactured according to the highest pharmaceutical standards for maximum safety and effectiveness. For more information, visit us at www.nativeremedies.com

Distributed by
Native Remedies, LLC
6531 Park of Commerce Blvd
Suite 160
Boca Raton, Fl 33487
Phone:+1.877.289.1235
International:+1.561.999.8857

Contains no artificial flavors or artificial colors. No gluten added.

STORAGE AND HANDLING

Tamper resistant for your protection. Use only if safety seal is intact.